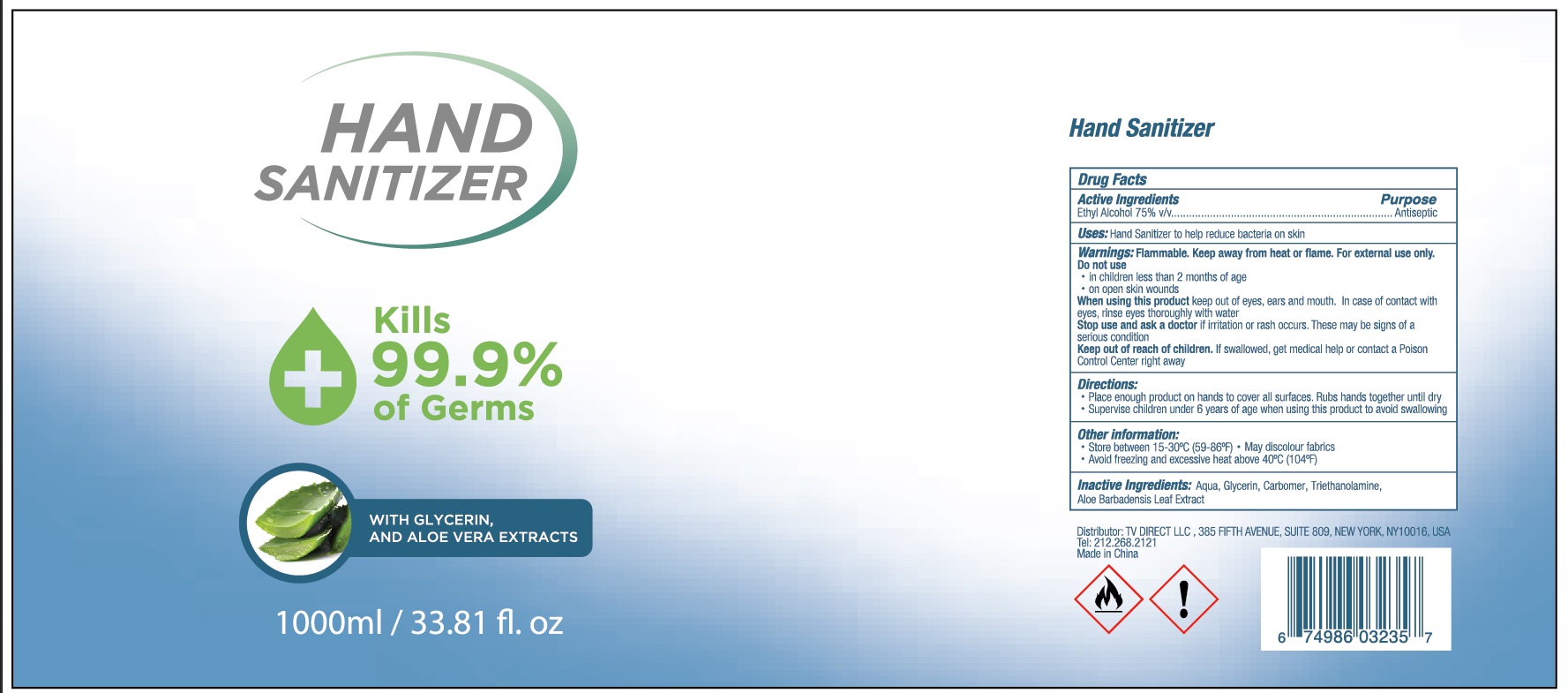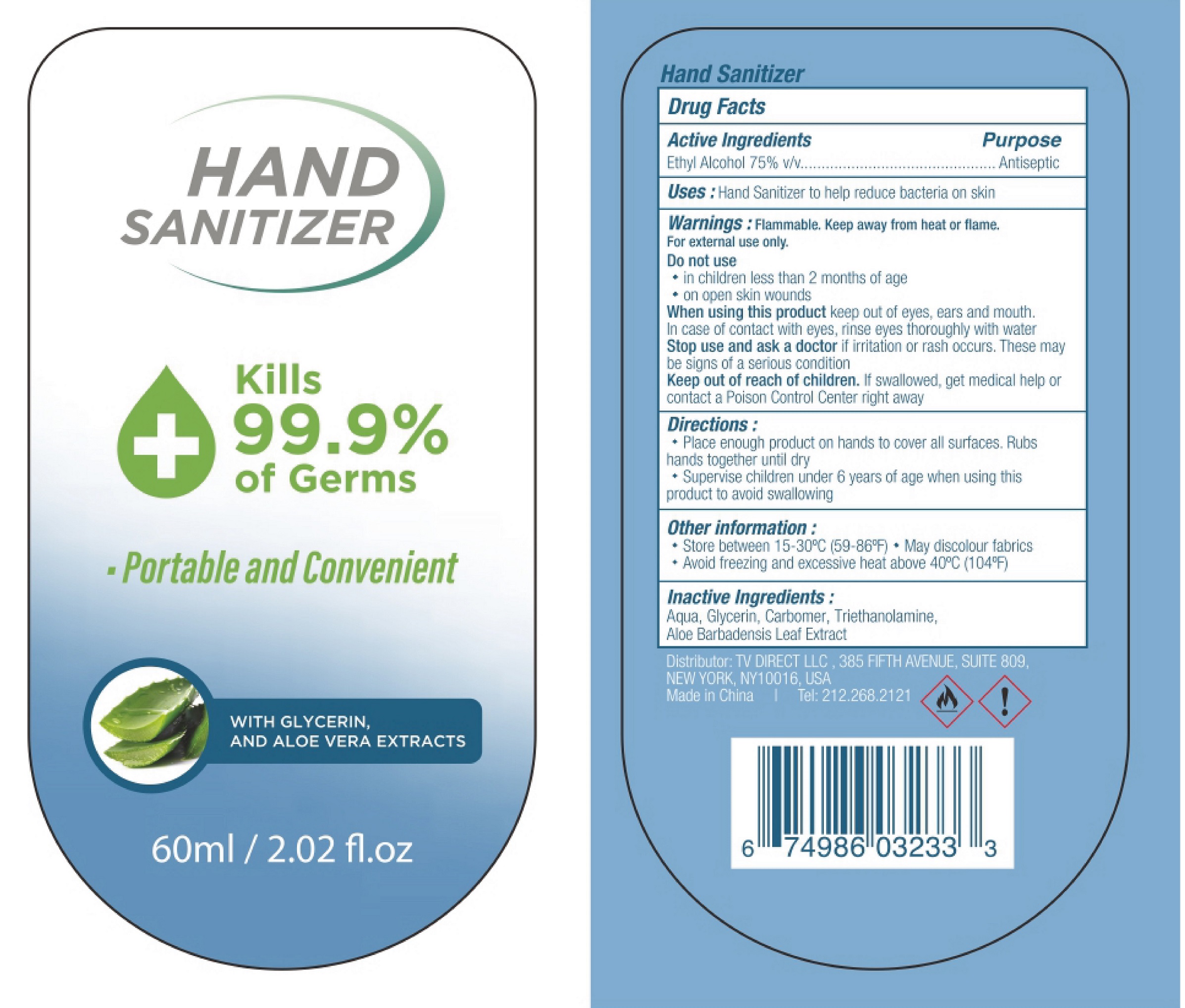 DRUG LABEL: Hand Sanitizer
NDC: 78915-001 | Form: GEL
Manufacturer: TV Direct LLC
Category: otc | Type: HUMAN OTC DRUG LABEL
Date: 20230223

ACTIVE INGREDIENTS: ALCOHOL 0.75 mL/1 mL
INACTIVE INGREDIENTS: WATER; GLYCERIN; CARBOMER HOMOPOLYMER, UNSPECIFIED TYPE; TROLAMINE; ALOE VERA LEAF

Hand Sanitizer

Active Ingredients

Ethyl Alcohol 75% v/v

Purpose

Antiseptic

Uses:

Hand Sanitizer to help reduce bacteria on the skin

Warnings:

Flammable. Keep away from heat or flame. For external use only.

Do not use

- in children less than 2 months of age
- on open skin wounds.

When using this product

keep out of eyes, ears, and mouth. In case of contact with eyes, rinse eyes thoroughly with water.

Stop use and ask a doctor

if irritation or rash occurs. These may be signs of a serious condition.

Keep out of reach of children.

If swallowed, get medical help or contact a Poison Control Center right away.

Directions:

- Place enough product on hands to cover all surfaces. Rubs hands together until dry.
- Supervise children under 6 years of age when using this product to avoid swallowing.

Other information:

- Store between 15-30°C (59-86°F)
- May discolor fabrics
- Avoid freezing and excessive heat above 40°C (104°F)

Inactive Ingredients:

Aqua, Glycerin, Carbomer, Triethanolamine, Aloe Barbadensis Leaf Extract